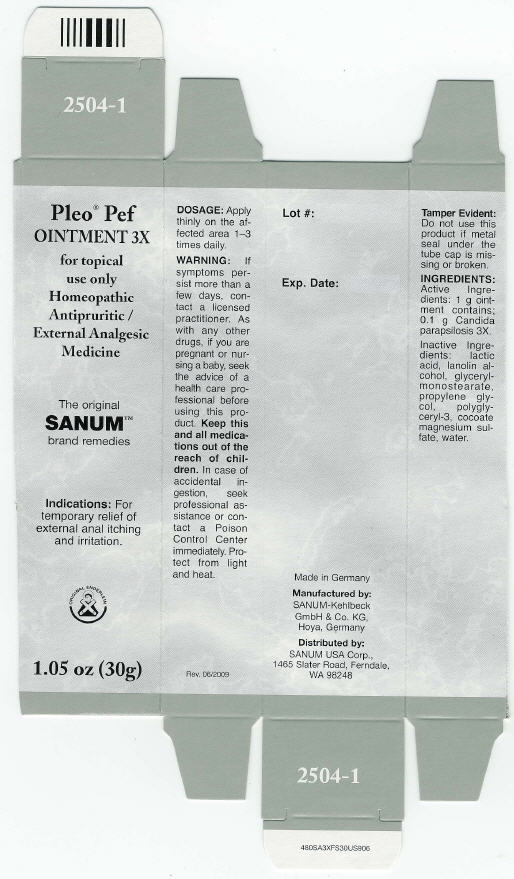 DRUG LABEL: Pleo Pef
NDC: 60681-2504 | Form: OINTMENT
Manufacturer: Sanum Kehlbeck GmbH & Co. KG
Category: homeopathic | Type: HUMAN OTC DRUG LABEL
Date: 20091014

ACTIVE INGREDIENTS: candida parapsilosis 3 [HP_X]/30 g
INACTIVE INGREDIENTS: glyceryl monostearate; lactic acid; propylene glycol; water

Pleo® Pef
OINTMENT 3X

for topical use only
Homeopathic Antipruritic / External Analgesic Medicine

1.05 oz (30g)

Indications

For temporary relief of external anal itching and irritation.

DOSAGE

Apply thinly on the affected area 1–3 times daily.

WARNING

If symptoms persist more than a few days, contact a licensed practitioner. As with any other drugs, if you are pregnant or nursing a baby, seek the advice of a health care professional before using this product.

KEEP OUT OF REACH OF CHILDREN

Keep this and all medications out of the reach of children. In case of accidental ingestion, seek professional assistance or contact a Poison Control Center immediately.

STORAGE AND HANDLING

Protect from light and heat.

Tamper Evident

Do not use this product if metal seal under the tube cap is missing or broken.

INGREDIENTS

Active Ingredients

1 g ointment contains; 0.1 g Candida parapsilosis 3X.

Inactive Ingredients

lactic acid, lanolin alcohol, glycerylmonostearate, propylene glycol, polyglyceryl-3, cocoate magnesium sulfate, water.

Made in Germany

Manufactured by:
SANUM-Kehlbeck
GmbH & Co. KG,
Hoya, Germany

Distributed by:
SANUM USA Corp.,
1465 Slater Road, Ferndale,
WA 98248

Rev. 06/2009

PRINCIPAL DISPLAY PANEL - 30 g Ointment Carton

Pleo® Pef
OINTMENT 3X

for topical
use only
Homeopathic
Antipruritic /
External Analgesic
Medicine

The original
SANUM™
brand remedies

Indications: For
temporary relief of
external anal itching
and irritation.

ORIGINAL ENDERLEIN

1.05 oz (30g)